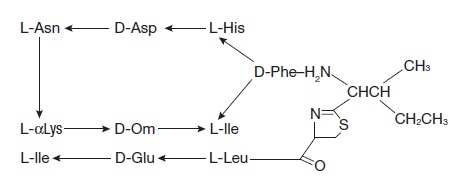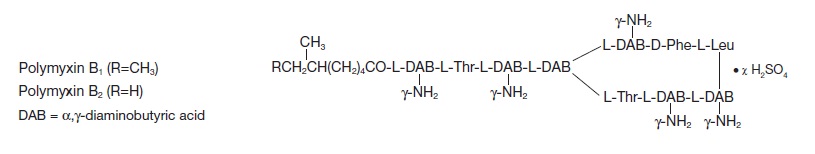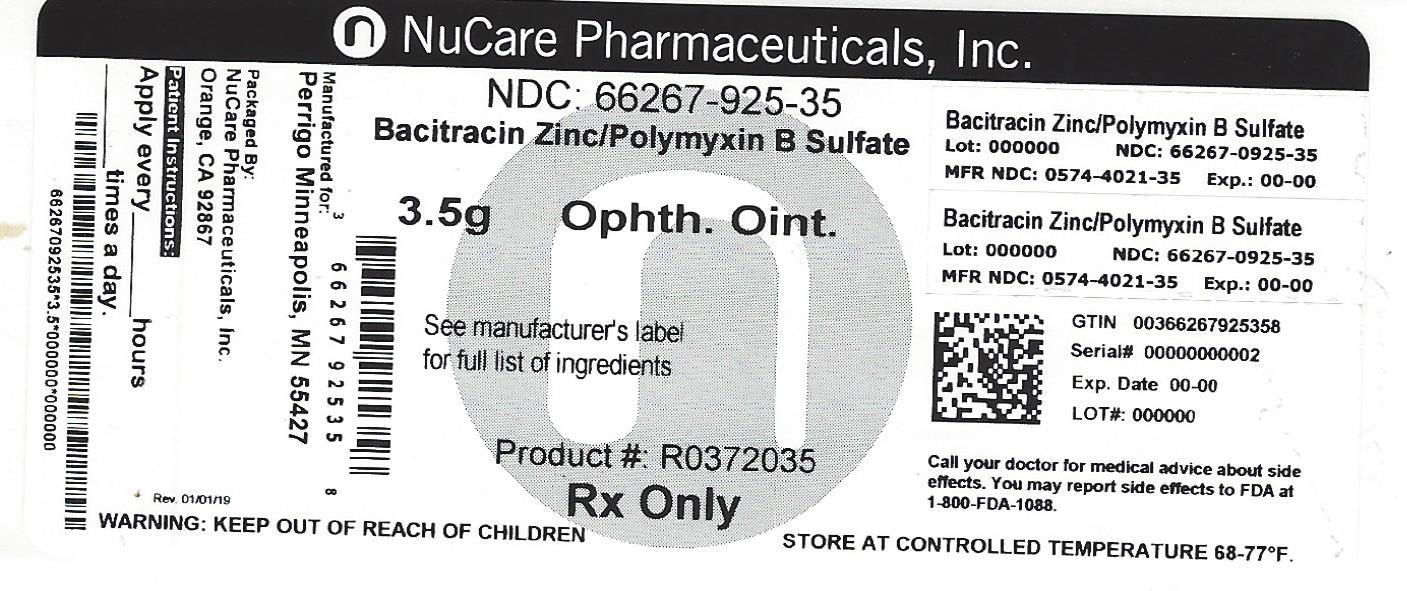 DRUG LABEL: polycin
NDC: 66267-925 | Form: OINTMENT
Manufacturer: NuCare Pharmaceuticals,Inc.
Category: prescription | Type: HUMAN PRESCRIPTION DRUG LABEL
Date: 20240814

ACTIVE INGREDIENTS: BACITRACIN ZINC 500 [USP'U]/1 g; POLYMYXIN B SULFATE 10000 [USP'U]/1 g
INACTIVE INGREDIENTS: PETROLATUM; MINERAL OIL

Polycin®
bacitracin zinc and polymyxin B sulfate Ophthalmic Ointment USP
STERILE Rx Only

DESCRIPTION:

Bacitracin Zinc and Polymyxin B Sulfate Ophthalmic Ointment USP, is a sterile antimicrobial ointment for ophthalmic use. Each gram contains: bacitracin zinc equivalent to 500 bacitracin units, polymyxin B sulfate equivalent to 10,000 polymyxin B units, mineral oil, and white petrolatum.

Bacitracin zinc is the zinc salt of bacitracin, a mixture of related cyclic polypeptides (mainly bacitracin A) produced by the growth of an organism of the licheniformisgroup of Bacillus subtilisvar Tracy. It has a potency of not less than 40 bacitracin units per mg. The structural formula for bacitracin A is:

Polymyxin B sulfate is the sulfate salt of polymyxin B1 and B2 which are produced by the growth of Bacillus polymyxa (Prazmowski) Migula (Fam. Bacillaceae). It has a potency of not less than 6,000 polymyxin B units per mg, calculated on an anhydrous basis. The structural formulae are:

CLINICAL PHARMACOLOGY:

A wide range of antibacterial action is provided by the overlapping spectra of bacitracin and polymyxin B sulfate. Bacitracin is bactericidal for a variety of gram-positive and gram-negative organisms. It interferes with bacterial cell wall synthesis by inhibition of the regeneration of phospholipid receptors involved in peptidoglycan synthesis. Polymyxin B is bactericidal for a variety of gram-negative organisms. It increases the permeability of the bacterial cell membrane by interacting with the phospholipid components of the membrane.

MICROBIOLOGY:

Bacitracin zinc and polymyxin B sulfate together are considered active against the following microorganisms: Staphylococcus aureus, streptococci including Streptococcus pneumoniae, Escherichia coli, Haemophilusinfluenzae, Klebsiella/Enterobacterspecies, Neisseria species and Pseudomonas aeruginosa. The product does not provide adequate coverage against Serratiamarcescens.

INDICATIONS AND USAGE:

Polycin® Ophthalmic Ointment is indicated for the topical treatment of superficial infections of the external eye and its adnexa caused by susceptible bacteria. Such infections encompass conjunctivitis, keratitis and keratoconjunctivitis, blepharitis and blepharoconjunctivitis.

CONTRAINDICATIONS:

Polycin® Ophthalmic Ointment is contraindicated in individuals who have shown hypersensitivity to any of its components.

WARNINGS:

NOT FOR INJECTION INTO THE EYE. Bacitracin Zinc and Polymyxin B Sulfate Ophthalmic Ointment should never be directly introduced into the anterior chamber of the eye. Ophthalmic ointments may retard corneal wound healing. Topical antibiotics may cause cutaneous sensitization. A precise incidence of hypersensitivity reactions (primarily skin rash) due to topical antibiotics is not known. The manifestations of sensitization to topical antibiotics are usually itching, reddening, and edema of the conjunctiva and eyelid. A sensitization reaction may manifest simply, as a failure to heal. During long-term use of topical antibiotic products, periodic examination for such signs is advisable, and the patient should be told to discontinue the product if they are observed. Symptoms usually subside quickly on withdrawing the medication. Application of products containing these ingredients should be avoided for the patient thereafter (see PRECAUTIONS: General).

PRECAUTIONS:

General:

As with other antibiotic preparations, prolonged use of Bacitracin Zinc and Polymyxin B Sulfate Ophthalmic Ointment may result in overgrowth of non susceptible organisms including fungi. If superinfection occurs, appropriate measures should be initiated. Bacterial resistance to Bacitracin Zinc and Polymyxin B Sulfate Ophthalmic Ointment may also develop. If purulent discharge, inflammation, or pain become aggravated, the patient should discontinue use of the medication and consult a physician.

There have been reports of bacterial keratitis associated with the use of topical ophthalmic products in multiple-dose containers which have been inadvertently contaminated by patients, most of whom has a concurrent corneal disease or a disruption of the ocular epithelial surface (see PRECAUTIONS: Information for Patients).

Allergic cross-reactions may occur which could prevent the use of any or all of the following antibiotics for the treatment of future infections: kanamycin, paromomycin, streptomycin, and possibly gentamicin.

Information for Patients:

Patients should be instructed to avoid allowing the tip of the dispensing container to contact the eye, eyelid, fingers, or any other surface. The use of this product by more than one person may spread infection.

Patients should also be instructed that ocular products, if handled improperly, can become contaminated by common bacteria known to cause ocular infections. Serious damage to the eye and subsequent loss of vision may result from using contaminated products (see PRECAUTIONS: General).

If the condition persists or gets worse, or if a rash or allergic reaction develops, the patient should be advised to stop use and consult a physician. Do not use this product if you are allergic to any of the listed ingredients. Keep tightly closed when not in use. Keep out of reach of children.

Carcinogenesis, Mutagenesis, Impairment of Fertility:

Long-term studies in animals to evaluate carcinogenic or mutagenic potential have not been conducted with polymyxin B sulfate or bacitracin. Polymyxin B has been reported to impair the motility of equine sperm, but its effects on male or female fertility are unknown. No adverse effects on male or female fertility, litter size, or survival were observed in rabbits given bacitracin zinc 100 gm/ton of diet.

Pregnancy:

Teratorgenic Effects:

Pregnancy Category C.

Animal reproduction studies have not been conducted with polymyxin B sulfate or bacitracin. It is also not known whether Bacitracin Zinc and Polymyxin B Sulfate Ophthalmic Ointment can cause fetal harm when administered to a pregnant woman or can affect reproduction capacity. Bacitracin Zinc and Polymyxin B Sulfate Ophthalmic Ointment should be given to a pregnant woman only if clearly needed.

Nursing Mothers:

It is not known whether this drug is excreted in human milk. Because many drugs are excreted in human milk, caution should be exercised when Bacitracin Zinc and Polymyxin B Sulfate Ophthalmic Ointment is administered to a nursing woman.

Pediatric Use:

Safety and effectiveness in pediatric patients have not been established.

ADVERSE REACTIONS:

Adverse reactions have occurred with the anti-infective components Bacitracin Zinc and Polymyxin B Sulfate Ophthalmic Ointment. The exact incidence is not known. Reactions occurring most often are allergic sensitization reactions including itching, swelling, and conjunctival erythema (see WARNINGS). More serious hypersensitivity reactions, including anaphylaxis, have been reported rarely. Local irritation on instillation has also been reported.

To report SUSPECTED ADVERSE REACTIONS, contact Perrigo at 1-866-634-9120 or FDA at 1-800-FDA-1088 or www.fda.gov/medwatch.

DOSAGE AND ADMINISTRATION:

May be applied every 3 or 4 hours for 7 to 10 days, depending on the severity of the infection.

HOW SUPPLIED:

Polycin® Ophthalmic Ointment is supplied in 3.5 g (1/8 oz) sterile tamper evident tubes with ophthalmic tip.

NDC 66267-925-35 Box of 3.5 g

Store at 20°-25°C (68°-77°F) [see USP Controlled Room Temperature].

Polycin® is a Registered Trademark of Perrigo Company

Manufactured For Perrigo, Minneapolis, MN 55427

R1113

Ini1113

6U200 RC J1

Rev 12-13 A